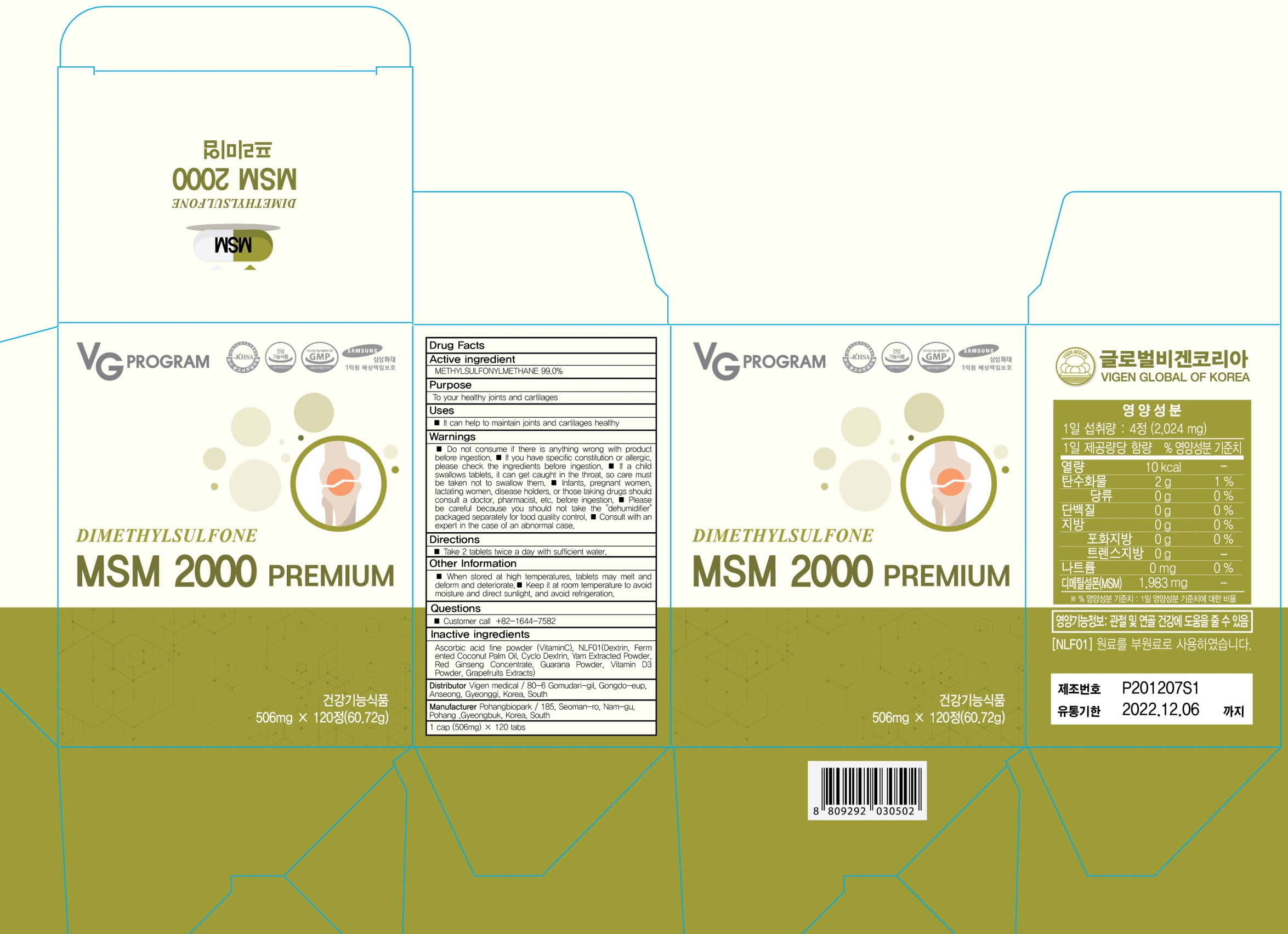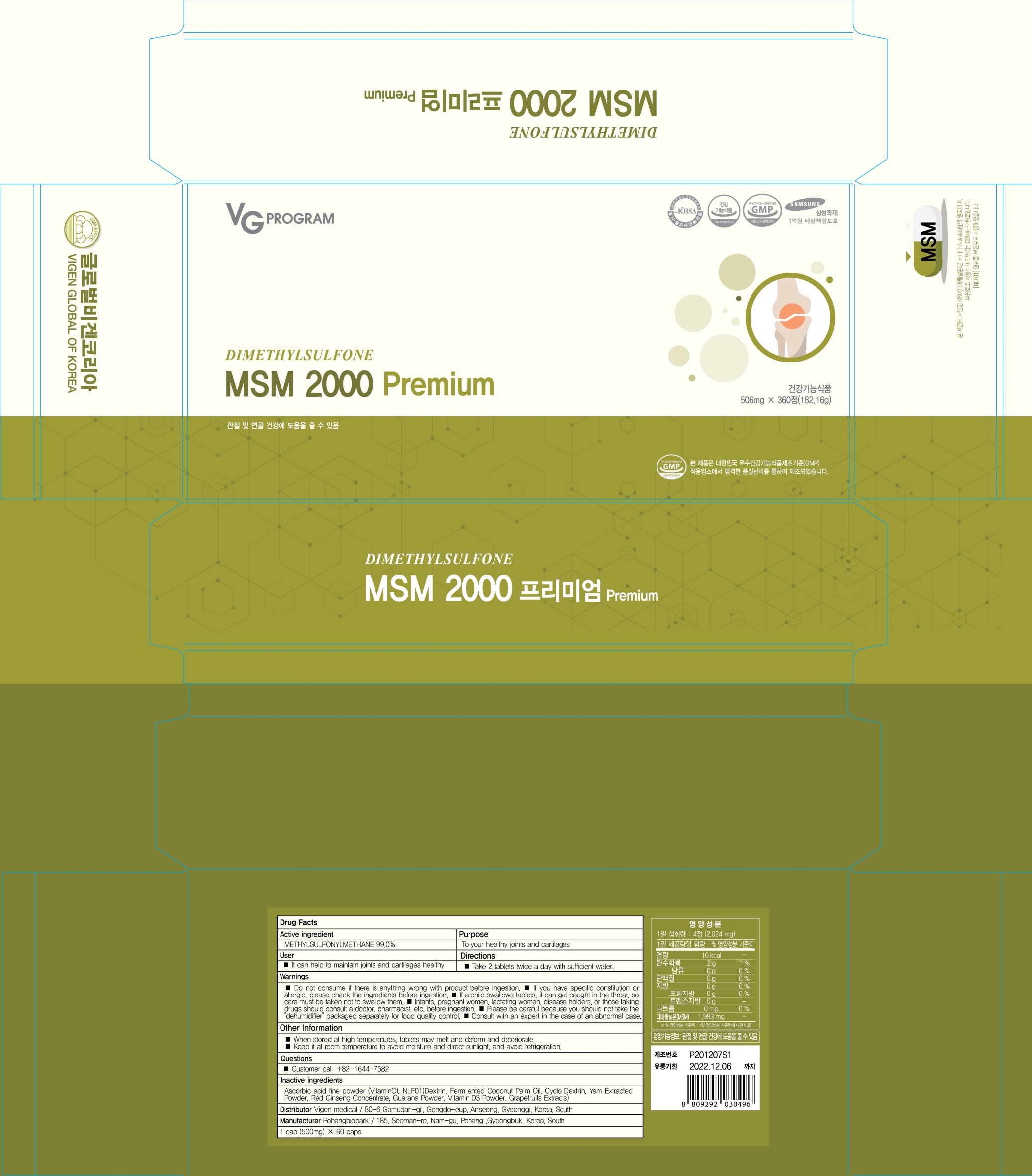 DRUG LABEL: MSM2000 Premium
NDC: 82437-020 | Form: TABLET
Manufacturer: Vigen medical
Category: otc | Type: HUMAN OTC DRUG LABEL
Date: 20211215

ACTIVE INGREDIENTS: DIMETHYL SULFONE 500 mg/506 mg
INACTIVE INGREDIENTS: ASCORBIC ACID

ACTIVE INGREDIENT

METHYLSULFONYLMETHANE 99.0%

INACTIVE INGREDIENTS

Ascorbic acid fine powder (VitaminC), NLF01(Dextrin, Fermented Coconut Palm Oil, Cyclo Dextrin, Yam Extracted Powder, Red Ginseng Concentrate, Guarana Powder, Vitamin D3 Powder, Grapefruits Extracts

PURPOSE

To your healthy joints and cartilages

WARNINGS

■ Do not consume if there is anything wrong with product before ingestion.
■ If you have specific constitution or allergic, please check the ingredients before ingestion.
■ If a child swallows tablets, it can get caught in the throat, so care must be taken not to swallow them.
■ Infants, pregnant women, lactating women, disease holders, or those taking drugs should consult a doctor, pharmacist, etc. before ingestion.
■ Please be careful because you should not take the "dehumidifier" packaged separately for food quality control.
■ Consult with an expert in the case of an abnormal case.

KEEP OUT OF REACH OF CHILDREN

Uses

■ It can help to maintain joints and cartilages healthy

Directions

■ Take 2 tablets twice a day with sufficient water.

Other Information

■ When stored at high temperatures, tablets may melt and deform and deteriorate.
■ Keep it at room temperature to avoid moisture and direct sunlight, and avoid refrigeration.

Questions

■ Customer call
+82-1644-7582